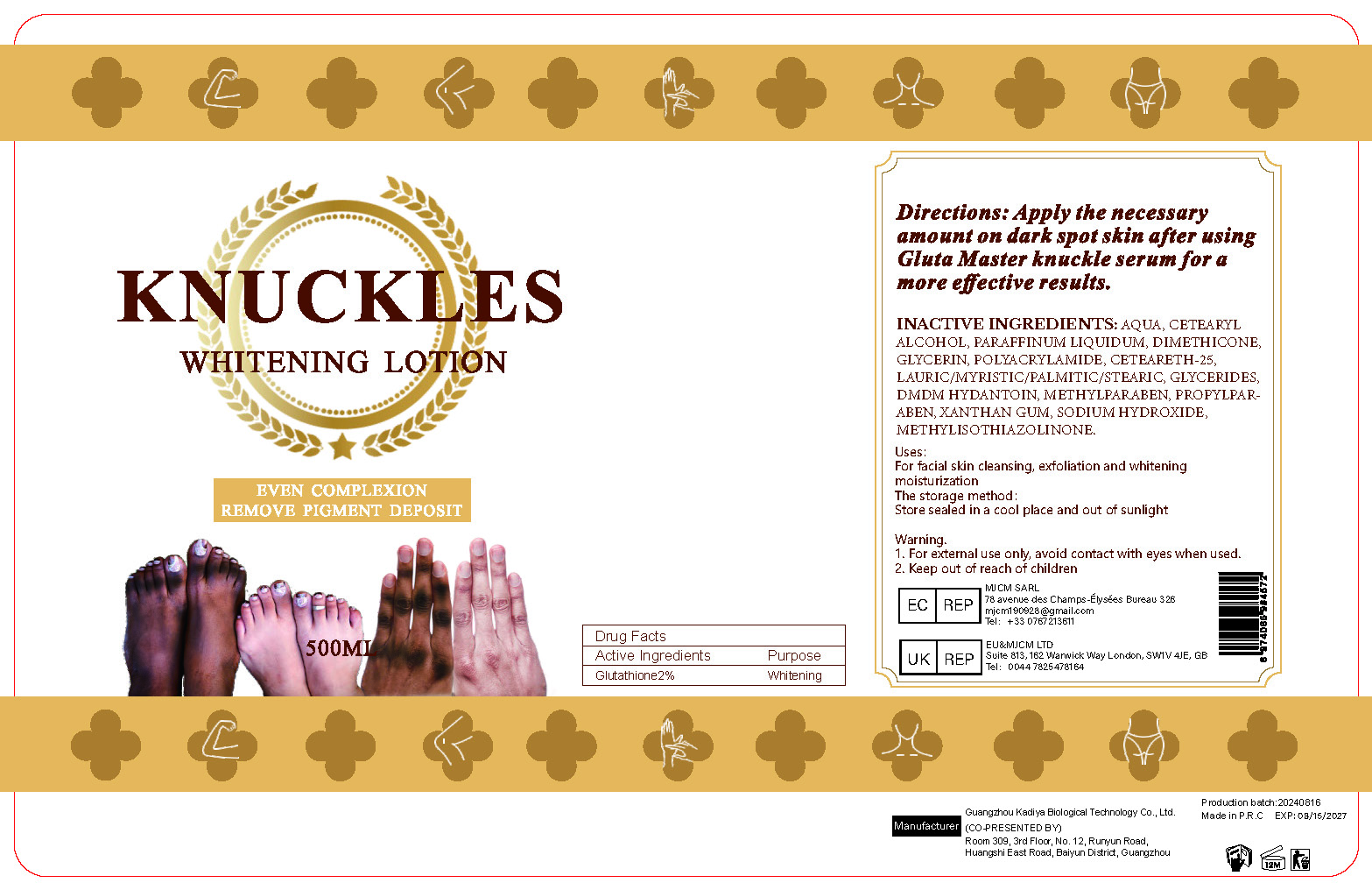 DRUG LABEL: Carrot BodyLotion
NDC: 84423-040 | Form: EMULSION
Manufacturer: Guangzhou Kadiya Biotechnology Co., Ltd.
Category: otc | Type: HUMAN OTC DRUG LABEL
Date: 20240827

ACTIVE INGREDIENTS: CARROT SEED OIL 10 mg/500 mL; ASCORBIC ACID 5 mg/500 mL; GLUTATHIONE 2.5 mg/500 mL
INACTIVE INGREDIENTS: XANTHAN GUM; SODIUM HYDROXIDE; DIMETHICONE; GLYCERIN; DMDM HYDANTOIN; METHYLPARABEN; METHYLISOTHIAZOLINONE; CETEARETH-25; MINERAL OIL; WATER; CETOSTEARYL ALCOHOL; PROPYLPARABEN; POLYACRYLAMIDE (10000 MW)

PURPOSE

For facial skin cleansing, exfoliation and whitening moisturization

INACTIVE INGREDIENT

AQUA、CETEARYL ALCOHOL、PARAFFINUM LIQUIDUM、DIMETHICONE、GLYCERIN、POLYACRYLAMIDE、CETEARETH-25、LAURIC/MYRISTIC/PALMITIC/STEARIC、GLYCERIDES、DMDM HYDANTOIN、METHYLPARABEN、PROPYLPARABEN、XANTHAN GUM、SODIUM HYDROXIDE、 METHYLISOTHIAZOLINONE

Warning.
1、For external use only, avoid contact with eyes when used
2、Keep out of reach of children

INDICATIONS AND USAGE

For facial skin cleansing, exfoliation and whitening moisturization

DOSAGE AND ADMINISTRATION

Apply a small quantity into a soft sponge or hands and massage all over the body, for best result use morning and evening.

ACTIVE INGREDIENT

Glutathione0.5%
ASCORBIC ACID1%
DAUCUS CAROTA FRUIT OIL2%

KEEP OUT OF REACH OF CHILDREN SECTION

PACKAGE LABEL

Active Ingredients
Glutathione0.5%
ASCORBIC ACID1%
DAUCUS CAROTA FRUIT OIL2%

Uses：
For facial skin cleansing, exfoliation and whitening moisturization
The storage method：
Store sealed in a cool place and out of sunlight

Warning.
1、For external use only, avoid contact with eyes when used
2、Keep out of reach of children

Inactive ingredients：
AQUA、CETEARYL ALCOHOL、PARAFFINUM LIQUIDUM、DIMETHICONE、GLYCERIN、POLYACRYLAMIDE、CETEARETH-25、LAURIC/MYRISTIC/PALMITIC/STEARIC、GLYCERIDES、DMDM HYDANTOIN、METHYLPARABEN、PROPYLPARABEN、XANTHAN GUM、SODIUM HYDROXIDE、 METHYLISOTHIAZOLINONE